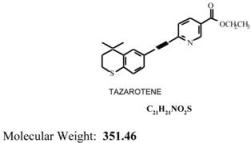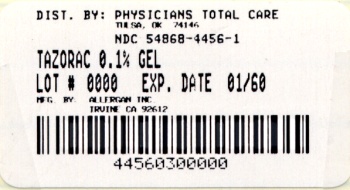 DRUG LABEL: Tazorac
NDC: 54868-4456 | Form: GEL
Manufacturer: Physicians Total Care, Inc.
Category: prescription | Type: HUMAN PRESCRIPTION DRUG LABEL
Date: 20101022

ACTIVE INGREDIENTS: TAZAROTENE 1 mg/1 g
INACTIVE INGREDIENTS: ASCORBIC ACID; BUTYLATED HYDROXYTOLUENE; CARBOMER HOMOPOLYMER TYPE B; EDETATE DISODIUM; HEXYLENE GLYCOL; POLOXAMER 407; POLYETHYLENE GLYCOL 400; POLYSORBATE 40; WATER; TROMETHAMINE

FOR DERMATOLOGIC USE ONLY

NOT FOR OPHTHALMIC, ORAL OR INTRAVAGINAL USE

DESCRIPTION

TAZORAC® Gel is a translucent, aqueous gel and contains the compound tazarotene, a member of the acetylenic class of retinoids. It is for topical dermatologic use only. The active ingredient is represented by the following structural formula:

Chemical Name:

Ethyl 6-[2-(4,4-dimethylthiochroman-6-yl) ethynyl] nicotinate

Contains:

Active: Tazarotene................................... 0.05% or 0.1% (w/w)
Preservative: Benzyl alcohol.................................. 1.0% (w/w)

Inactives: Ascorbic acid, butylated hydroxyanisole, butylated hydroxytoluene, carbomer 934P, edetate disodium, hexylene glycol, poloxamer 407, polyethylene glycol 400, polysorbate 40, purified water, and tromethamine.

CLINICAL PHARMACOLOGY

Tazarotene is a retinoid prodrug which is converted to its active form, the cognate carboxylic acid of tazarotene (AGN 190299), by rapid deesterification in animals and man. AGN 190299 (“tazarotenic acid”) binds to all three members of the retinoic acid receptor (RAR) family: RARα, RARβ, and RARγ but shows relative selectivity for RARβ, and RARγ and may modify gene expression. The clinical significance of these findings is unknown.

Psoriasis: The mechanism of tazarotene action in psoriasis is not defined. Topical tazarotene blocks induction of mouse epidermal ornithine decarboxylase (ODC) activity, which is associated with cell proliferation and hyperplasia. In cell culture and in vitro models of skin, tazarotene suppresses expression of MRP8, a marker of inflammation present in the epidermis of psoriasis patients at high levels. In human keratinocyte cultures, it inhibits cornified envelope formation, whose build-up is an element of the psoriatic scale. Tazarotene also induces the expression of a gene which may be a growth suppressor in human keratinocytes and which may inhibit epidermal hyperproliferation in treated plaques. However, the clinical significance of these findings is unknown.

Acne: The mechanism of tazarotene action in acne vulgaris is not defined. However, the basis of tazarotene's therapeutic effect in acne may be due to its anti-hyperproliferative, normalizing-of-differentiation and anti-inflammatory effects. Tazarotene inhibited corneocyte accumulation in rhino mouse skin and cross-linked envelope formation in cultured human keratinocytes. The clinical significance of these findings is unknown.

Pharmacokinetics:

Following topical application, tazarotene undergoes esterase hydrolysis to form its active metabolite, tazarotenic acid. Little parent compound could be detected in the plasma. Tazarotenic acid was highly bound to plasma proteins (>99%). Tazarotene and tazarotenic acid were metabolized to sulfoxides, sulfones and other polar metabolites which were eliminated through urinary and fecal pathways. The half-life of tazarotenic acid was approximately 18 hours, following topical application of tazarotene to normal, acne or psoriatic skin.

The human in vivo studies described below were conducted with tazarotene gel applied topically at approximately 2 mg/cm^2 and left on the skin for 10 to 12 hours. Both the peak plasma concentration (Cmax) and area under the plasma concentration time curve (AUC) refer to the active metabolite only.

Two single, topical dose studies were conducted using ^14C-tazarotene gel. Systemic absorption, as determined from radioactivity in the excreta, was less than 1% of the applied dose (without occlusion) in six psoriatic patients and approximately 5% of the applied dose (under occlusion) in six healthy subjects. One non-radiolabeled single-dose study comparing the 0.05% gel to the 0.1% gel in healthy subjects indicated that the Cmax and AUC were 40% higher for the 0.1% gel.

After 7 days of topical dosing with measured doses of tazarotene 0.1% gel on 20% of the total body surface without occlusion in 24 healthy subjects, the Cmax for tazarotenic acid was 0.72 ± 0.58 ng/mL (mean ± SD) occurring 9 hours after the last dose, and the AUC0-24hr for tazarotenic acid was 10.1 ± 7.2 ng·hr/mL. Systemic absorption was 0.91 ± 0.67% of the applied dose.

In a 14-day study in five psoriatic patients, measured doses of tazarotene 0.1% gel were applied daily by nursing staff to involved skin without occlusion (8 to 18% of total body surface area; mean ± SD: 13 ± 5%). The Cmax for tazarotenic acid was 12.0 ± 7.6 ng/mL occurring 6 hours after the final dose, and the AUC0-24hr for tazarotenic acid was 105 ± 55 ng·hr/mL. Systemic absorption was 14.8 ± 7.6% of the applied dose. Extrapolation of these results to represent dosing on 20% of total body surface yielded estimates for tazarotenic acid with Cmax of 18.9 ± 10.6 ng/mL and AUC0-24hr of 172 ± 88 ng·hr/mL.

An in vitro percutaneous absorption study, using radiolabeled drug and freshly excised human skin or human cadaver skin, indicated that approximately 4 to 5% of the applied dose was in the stratum corneum (tazarotene: tazarotenic acid= 5:1) and 2 to 4% was in the viable epidermis-dermis layer (tazarotene: tazarotenic acid= 2:1) 24 hours after topical application of the gel.

CLINICAL STUDIES

Psoriasis:

In two large vehicle-controlled clinical studies, tazarotene 0.05% and 0.1% gels applied once daily for 12 weeks were significantly more effective than vehicle in reducing the severity of the clinical signs of stable plaque psoriasis covering up to 20% of body surface area. In one of the studies, patients were followed up for an additional 12 weeks following cessation of therapy with TAZORAC® Gel. Mean baseline scores and changes from baseline (reductions) after treatment in these two studies are shown in the following Table:

Plaque Elevation, Scaling and Erythema in Two Controlled Clinical Trials for Psoriasis
 |  | TAZORAC® 0.05% Gel | TAZORAC® 0.1% Gel | Vehicle Gel
 |  | Trunk/Arm/ Leg lesions | Knee/Elbow lesions | Trunk/Arm/ Leg lesions | Knee/Elbow lesions | Trunk/Arm/ Leg lesions | Knee/Elbow lesions
 |  | N=108 | N=111 | N=108 | N=111 | N=108 | N=112 | N=108 | N=112 | N=108 | N=113 | N=108 | N=113
Plaque elevation | B* C-12* C-24* | 2.5 -1.4 -1.2 | 2.6 -1.3 | 2.6 -1.3 -1.1 | 2.6 -1.1 | 2.5 -1.4 -1.1 | 2.6 -1.4 | 2.6 -1.5 -1.0 | 2.6 -1.3 | 2.4 -0.8 -0.9 | 2.6 -0.7 | 2.6 -0.7 -0.7 | 2.6 -0.6
Scaling | B* C-12* C-24* | 2.4 -1.1 -0.9 | 2.5 -1.1 | 2.5 -1.1 -0.8 | 2.6 -0.9 | 2.4 -1.3 -1.0 | 2.6 -1.3 | 2.5 -1.2 -0.8 | 2.7 -1.2 | 2.4 -0.7 -0.8 | 2.6 -0.7 | 2.5 -0.6 -0.7 | 2.7 -0.6
Erythema | B* C-12* C-24* | 2.4 -1.0 -1.1 | 2.7 -0.8 | 2.2 -0.9 -0.7 | 2.5 -0.8 | 2.4 -1.0 -0.9 | 2.8 -1.1 | 2.3 -1.0 -0.8 | 2.5 -0.8 | 2.3 -0.6 -0.7 | 2.7 -0.5 | 2.2 -0.5 -0.6 | 2.5 -0.5

Plaque elevation, scaling and erythema scored on a 0-4 scale with 0=none, 1=mild, 2=moderate, 3=severe and 4=very severe.
*B=Mean Baseline Severity: C-12=Mean Change from Baseline at end of 12 weeks of therapy:
C-24=Mean Change from Baseline at week 24 (12 weeks after the end of therapy).

Global improvement over baseline at the end of 12 weeks of treatment in these two studies is shown in the following Table:

 | TAZORAC® 0.05% Gel | TAZORAC® 0.1% Gel | Vehicle Gel
 | N=81 | N=93 | N=79 | N=69 | N=84 | N=91
100% improvement | 2 (2%) | 1(1%) | 0 | 0 | 1 (1%) | 0
≥75% improvement | 23 (28%) | 17 (18%) | 30 (38%) | 17 (25%) | 10 (12%) | 9 (10%)
≥50% improvement | 42 (52%) | 39 (42%) | 51 (65%) | 36 (52%) | 28 (33%) | 21 (23%)
1-49% improvement | 21 (26%) | 32 (34%) | 18 (23%) | 23 (33%) | 27 (32%) | 32 (35%)
No change or worse | 18 (22%) | 22 (24%) | 10 (13%) | 10 (14%) | 29 (35%) | 38 (42%)

The 0.1% gel was more effective than the 0.05% gel, but the 0.05% gel was associated with less local irritation than the 0.1% gel (see ADVERSE REACTIONS section).

Acne:

In two large vehicle-controlled studies, tazarotene 0.1% gel applied once daily was significantly more effective than vehicle in the treatment of facial acne vulgaris of mild to moderate severity. Percent reductions in lesion counts after treatment for 12 weeks in these two studies are shown in the following Table:

Reduction in Lesion Counts after Twelve Weeks of Treatment in Two Controlled Clinical Trials for Acne
 | TAZORAC® 0.1% Gel | Vehicle Gel
 | N=150 | N=149 | N=148 | N=149
Noninflammatory lesions | 55% | 43% | 35% | 27%
Inflammatory lesions | 42% | 47% | 30% | 28%
Total lesions | 52% | 45% | 33% | 27%

Global improvement over baseline at the end of 12 weeks of treatment in these two studies is shown in the following Table:

 | TAZORAC® 0.1% Gel | Vehicle Gel
 | N=105 | N=117 | N=117 | N=110
100% improvement | 1 (1%) | 0 | 0 | 0
≥75% improvement | 40 (38%) | 21 (18%) | 23 (20%) | 11 (10%)
≥50% improvement | 71 (68%) | 56 (48%) | 47 (40%) | 32 (29%)
1-49% improvement | 23 (22%) | 49 (42%) | 48 (41%) | 46 (42%)
No change or worse | 11 (10%) | 12 (10%) | 22 (19%) | 32 (29%)

INDICATIONS AND USAGE

TAZORAC® (tazarotene) Gel 0.05% and 0.1% are indicated for the topical treatment of patients with stable plaque psoriasis of up to 20% body surface area involvement.

TAZORAC® (tazarotene) Gel 0.1% is also indicated for the topical treatment of patients with facial acne vulgaris of mild to moderate severity.

The efficacy of TAZORAC® Gel in the treatment of acne previously treated with other retinoids or resistant to oral antibiotics has not been established.

CONTRAINDICATIONS

Retinoids may cause fetal harm when administered to a pregnant woman.

In rats, tazarotene 0.05% gel, administered topically during gestation days 6 through 17 at 0.25 mg/kg/day (1.5 mg/m^2/day) resulted in reduced fetal body weights and reduced skeletal ossification. Rabbits dosed topically with 0.25 mg/kg/day (2.75 mg/m^2 total body surface area/day) tazarotene gel during gestation days 6 through 18 were noted with single incidences of known retinoid malformations, including spina bifida, hydrocephaly, and heart anomalies. Systemic daily-exposure (AUCde) to tazarotenic acid at topical doses of 0.25 mg/kg/day tazarotene in a gel formulation in rats and rabbits represented 0.62 and 6.7 times, respectively, the AUC0-24h observed in psoriatic patients treated with 2 mg/cm^2 of tazarotene gel 0.1% (extrapolated for topical application over 20% body surface area), and 0.78 and 8.4 times, respectively, the maximum AUC0-24h in acne patients treated with 2 mg/cm^2 of tazarotene gel 0.1% over 15% (targeted) body surface area.

As with other retinoids, when tazarotene was given orally to experimental animals, developmental delays were seen in rats, and teratogenic effects and post-implantation loss were observed in rats and rabbits at AUCde values that were 0.55 and 13.2 times, respectively, the AUC0-24h observed in psoriatic patients treated with 2 mg/cm^2 of tazarotene gel 0.1% (extrapolated for topical application over 20% body surface area), and 0.68 and 16.4 times, respectively, the maximum AUC0-24h in acne patients treated with 2 mg/cm^2 of tazarotene gel 0.1% over 15% (targeted) body surface area.

In a study of the effect of oral tazarotene on fertility and early embryonic development in rats, decreased number of implantation sites, decreased litter size, decreased numbers of live fetuses, and decreased fetal body weights, all classic developmental effects of retinoids, were observed when female rats were administered 2 mg/kg/day from 15 days before mating through gestation day 7. A low incidence of retinoid-related malformations at that dose was reported to be related to treatment. This dose produced an AUCde that was 1.7 times the AUC0-24h observed in psoriatic patients treated with 2 mg/cm^2 tazarotene gel 0.1% (extrapolated for topical application over 20% body surface area) and 2.1 times the maximum AUC0-24h in acne patients treated with 2 mg/cm^2 of tazarotene gel 0.1% over 15% (targeted) body surface area.

SYSTEMIC EXPOSURE TO TAZAROTENIC ACID IS DEPENDENT UPON THE EXTENT OF THE BODY SURFACE AREA TREATED. IN PATIENTS TREATED TOPICALLY OVER SUFFICIENT BODY SURFACE AREA, EXPOSURE COULD BE IN THE SAME ORDER OF MAGNITUDE AS IN THESE ORALLY TREATED ANIMALS. ALTHOUGH THERE MAY BE LESS SYSTEMIC EXPOSURE IN THE TREATMENT OF ACNE OF THE FACE ALONE DUE TO LESS SURFACE AREA FOR APPLICATION, TAZAROTENE IS A TERATOGENIC SUBSTANCE, AND IT IS NOT KNOWN WHAT LEVEL OF EXPOSURE IS REQUIRED FOR TERATOGENICITY IN HUMANS (SEE CLINICAL PHARMACOLOGY: PHARMACOKINETICS).

There were thirteen reported pregnancies in patients who participated in clinical trials for topical tazarotene. Nine of the patients were found to have been treated with topical tazarotene, and the other four had been treated with vehicle. One of the patients who was treated with tazarotene cream elected to terminate the pregnancy for non-medical reasons unrelated to treatment. The other eight pregnant women who were inadvertently exposed to topical tazarotene during clinical trials subsequently delivered apparently healthy babies. As the exact timing and extent of exposure in relation to the gestation times are not certain, the significance of these findings is unknown.

TAZORAC® Gel is contraindicated in women who are or may become pregnant. If this drug is used during pregnancy, or if the patient becomes pregnant while taking this drug, treatment should be discontinued and the patient apprised of the potential hazard to the fetus. Women of child-bearing potential should be warned of the potential risk and use adequate birth-control measures when TAZORAC® Gel is used. The possibility that a woman of childbearing potential is pregnant at the time of institution of therapy should be considered. A negative result for pregnancy test having a sensitivity down to at least 50 mIU/mL for human chorionic gonadotropin (hCG) should be obtained within 2 weeks prior to TAZORAC® Gel therapy, which should begin during a normal menstrual period (see also PRECAUTIONS: Pregnancy: Teratogenic Effects).

TAZORAC® Gel is contraindicated in individuals who have shown hypersensitivity to any of its components.

WARNINGS

Pregnancy Category X. See CONTRAINDICATIONS section. Women of child-bearing potential should be warned of the potential risk and use adequate birth-control measures when TAZORAC® Gel is used. The possibility that a woman of childbearing potential is pregnant at the time of institution of therapy should be considered. A negative result for pregnancy test having a sensitivity down to at least 50 mIU/mL for hCG should be obtained within 2 weeks prior to TAZORAC® Gel therapy, which should begin during a normal menstrual period.

PRECAUTIONS

General:

TAZORAC® Gel should be applied only to the affected areas. For external use only. Avoid contact with eyes, eyelids, and mouth. If contact with eyes occurs, rinse thoroughly with water. The safety of use of TAZORAC® Gel over more than 20% of body surface area has not been established in psoriasis or acne.

Retinoids should not be used on eczematous skin, as they may cause severe irritation.

Because of heightened burning susceptibility, exposure to sunlight (including sunlamps) should be avoided unless deemed medically necessary, and in such cases, exposure should be minimized during the use of TAZORAC® Gel. Patients must be warned to use sunscreens (minimum SPF of 15) and protective clothing when using TAZORAC® Gel. Patients with sunburn should be advised not to use TAZORAC® Gel until fully recovered. Patients who may have considerable sun exposure due to their occupation and those patients with inherent sensitivity to sunlight should exercise particular caution when using TAZORAC® Gel and ensure that the precautions outlined in the Information for Patients subsection are observed.

TAZORAC® Gel should be administered with caution if the patient is also taking drugs known to be photosensitizers (e.g., thiazides, tetracyclines, fluoroquinolones, phenothiazines, sulfonamides) because of the increased possibility of augmented photosensitivity.

Some individuals may experience excessive pruritus, burning, skin redness or peeling. If these effects occur, the medication should either be discontinued until the integrity of the skin is restored, or the dosing should be reduced to an interval the patient can tolerate. However, efficacy at reduced frequency of application has not been established. Alternatively, patients with psoriasis who are being treated with the 0.1% concentration can be switched to the lower concentration.

Weather extremes, such as wind or cold, may be more irritating to patients using TAZORAC® Gel.

Information for Patients:

See attached Patient Package Insert.

Drug Interactions:

Concomitant dermatologic medications and cosmetics that have a strong drying effect should be avoided. It is also advisable to "rest" a patient's skin until the effects of such preparations subside before use of TAZORAC® Gel is begun.

Carcinogenesis, Mutagenesis, Impairment of Fertility:

A long-term study of tazarotene following oral administration of 0.025, 0.050, and 0.125 mg/kg/day to rats showed no indications of increased carcinogenic risks. Based on pharmacokinetic data from a shorter-term study in rats, the highest dose of 0.125 mg/kg/day was anticipated to give systemic exposure (AUCde) in the rat equivalent to 0.32 times the AUC0-24h observed in psoriatic patients treated with 2 mg/cm^2 of tazarotene gel 0.1% (extrapolated for topical application over 20% body surface area), and 0.38 times the maximum AUC0-24h in acne patients treated with 2 mg/cm^2 of tazarotene gel 0.1% over 15% (targeted) body surface area.

In evaluation of photo co-carcinogenicity, median time to onset of tumors was decreased, and the number of tumors increased in hairless mice following chronic topical dosing with intercurrent exposure to ultraviolet radiation at tazarotene concentrations of 0.001%, 0.005%, and 0.01% in a gel formulation for up to 40 weeks.

A long-term topical application study of up to 0.1% tazarotene in a gel formulation in mice terminated at 88 weeks showed that dose levels of 0.05, 0.125, 0.25, and 1.0 mg/kg/day (reduced to 0.5 mg/kg/day for males after 41 weeks due to severe dermal irritation) revealed no apparent carcinogenic effects when compared to vehicle control animals; untreated control animals were not completely evaluated. Systemic exposure (AUC0-12h) at the highest dose was 2.0 times the AUC0-24h observed in psoriatic patients treated with 2 mg/cm^2 of tazarotene gel 0.1% (extrapolated for topical application over 20% body surface area), and 2.5 times the maximum AUC0-24h in acne patients treated with 2 mg/cm ^2 of tazarotene gel 0.1% over 15 % (targeted) body surface area.

Tazarotene was found to be non-mutagenic in the Ames assay using Salmonella and E. coli and did not produce structural chromosomal aberrations in a human lymphocyte assay. Tazarotene was also non-mutagenic in the CHO/HGPRT mammalian cell forward gene mutation assay and was non-clastogenic in the in vivo mouse micronucleus test.

No impairment of fertility occurred in rats when male animals were treated for 70 days prior to mating and female animals were treated for 14 days prior to mating and continuing through gestation and lactation with topical doses of tazarotene gel up to 0.125 mg/kg/day. Based on data from another study, the systemic drug exposure (AUCde) in the rat would be equivalent to 0.31 times the AUC0-24h observed in psoriatic patients treated with 2 mg/cm^2 of tazarotene gel 0.1% (extrapolated for topical application over 20% body surface area), and 0.38 times the maximum AUC0-24h in acne patients treated with 2 mg/cm^2 of tazarotene gel 0.1% over 15 % (targeted) body surface area.

No impairment of mating performance or fertility was observed in male rats treated for 70 days prior to mating with oral doses of up to 1.0 mg/kg/day tazarotene, which produced an AUCde that was 0.95 times the AUC0-24h observed in psoriatic patients treated with 2 mg/cm^2 of tazarotene gel 0.1% (extrapolated for topical application over 20% body surface area), and 1.2 times the maximum AUC0-24h in acne patients treated with 2 mg/cm^2 of tazarotene gel 0.1% over 15 % (targeted) body surface area.

No effect on parameters of mating performance or fertility was observed in female rats treated for 15 days prior to mating and continuing through day 7 of gestation with oral doses of tazarotene up to 2.0 mg/kg/day. However, there was a significant decrease in the number of estrous stages and an increase in developmental effects at 2.0 mg/kg/day (see CONTRAINDICATIONS). This dose produced an AUC0-24h which was 1.7 times that observed in psoriatic patients treated with 2 mg/cm^2 of tazarotene gel 0.1% (extrapolated for topical application over 20% body surface area), and 2.1 times the maximum AUC0-24h in acne patients treated with 2 mg/cm^2 of tazarotene gel 0.1% over 15% (targeted) body surface area.

Reproductive capabilities of F1 animals, including F2 survival and development, were not affected by topical administration of tazarotene gel to female F0 parental rats from gestation day 16 through lactation day 20 at the maximum tolerated dose of 0.125 mg/kg/day. Based on data from another study, the systemic drug exposure (AUCde) in the rat would be equivalent to 0.31 times the AUC0-24h observed in psoriatic patients treated with 2 mg/cm^2 of tazarotene gel 0.1% (extrapolated for topical application over 20% body surface area), and 0.38 times the maximum AUC0-24h in acne patients treated with 2 mg/cm^2 of tazarotene gel 0.1% over 15% (targeted) body surface area.

Pregnancy:

Teratogenic Effects: Pregnancy Category X: See CONTRAINDICATIONS section. Women of child-bearing potential should use adequate birth-control measures when TAZORAC® Gel is used. The possibility that a woman of childbearing potential is pregnant at the time of institution of therapy should be considered. A negative result for pregnancy test having a sensitivity down to at least 50 mIU/mL for hCG should be obtained within 2 weeks prior to TAZORAC® Gel therapy, which should begin during a normal menstrual period. There are no adequate, well-controlled studies in pregnant women. Although there may be less systemic exposure in the treatment of acne of the face alone due to less surface area for application, tazarotene is a teratogenic substance , and it is not known what level of exposure is required for teratogenicity in humans (see CLINICAL PHARMACOLOGY: Pharmacokinetics).

Nursing mothers:

After single topical doses of ^14C-tazarotene to the skin of lactating rats, radioactivity was detected in milk, suggesting that there would be transfer of drug-related material to the offspring via milk. It is not known whether this drug is excreted in human milk. Caution should be exercised when tazarotene is administered to a nursing woman.

Pediatric Use:

The safety and efficacy of tazarotene have not been established in pediatric patients under the age of 12 years.

Geriatric Use:

Of the total number of subjects in clinical studies of tazarotene gels, 0.05% and 0.1% for plaque psoriasis, 163 were over the age of 65. Subjects over 65 years of age experienced more adverse events and lower treatment success rates after 12 weeks of use of TAZORAC® Gel compared with those 65 years of age and younger. Currently there is no other reliable clinical experience on the differences in responses between the elderly and younger patients, but greater sensitivity of some older individuals can not be ruled out. Tazarotene gel for the treatment of acne has not been clinically evaluated in persons over the age of 65.

ADVERSE REACTIONS

In human dermal safety studies, tazarotene 0.05% and 0.1% gels did not induce allergic contact sensitization, phototoxicity or photoallergy.

Psoriasis:

The most frequent adverse events reported with TAZORAC® Gel 0.05% and 0.1% were limited to the skin. Those occurring in 10 to 30% of patients, in descending order, included pruritus, burning/stinging, erythema, worsening of psoriasis, irritation, and skin pain. Events occurring in 1 to 10% of patients included rash, desquamation, irritant contact dermatitis, skin inflammation, fissuring, bleeding and dry skin. Increases in “psoriasis worsening” and “sun-induced erythema” were noted in some patients over the 4th to 12th months as compared to the first three months of a 1 year study. In general, the incidence of adverse events with TAZORAC® Gel 0.05% was 2 to 5% lower than that seen with TAZORAC® Gel 0.1%.

Acne:

The most frequent adverse events reported with TAZORAC® Gel 0.1% in the treatment of acne occurring in 10 to 30% of patients, in descending order, included desquamation, burning/stinging, dry skin, erythema and pruritus. Events occurring in 1 to 10% of patients included irritation, skin pain, fissuring, localized edema and skin discoloration.

OVERDOSAGE

Excessive topical use of TAZORAC® Gel may lead to marked redness, peeling, or discomfort (see PRECAUTIONS: General).

TAZORAC® Gels 0.05% and 0.1% are not for oral use. Oral ingestion of the drug may lead to the same adverse effects as those associated with excessive oral intake of Vitamin A (hypervitaminosis A) or other retinoids. If oral ingestion occurs, the patient should be monitored, and appropriate supportive measures should be administered as necessary.

DOSAGE AND ADMINISTRATION

General:

Application may cause excessive irritation in the skin of certain sensitive individuals. In cases where it has been necessary to temporarily discontinue therapy, or the dosing has been reduced to a lower concentration (in patients with psoriasis) or to an interval the patient can tolerate, therapy can be resumed, or the drug concentration or frequency of application can be increased as the patient becomes able to tolerate the treatment. Frequency of application should be closely monitored by careful observation of the clinical therapeutic response and skin tolerance. Efficacy has not been established for less than once daily dosing frequencies.

For psoriasis: It is recommended that treatment start with TAZORAC® 0.05% Gel, with strength increased to 0.1% if tolerated and medically indicated. Apply TAZORAC® Gel once a day, in the evening, to psoriatic lesions, using enough (2 mg/cm^2) to cover only the lesion with a thin film to no more than 20% of body surface area. If a bath or shower is taken prior to application, the skin should be dry before applying the gel. If emollients are used, they should be applied at least an hour before application of TAZORAC® Gel. Because unaffected skin may be more susceptible to irritation, application of tazarotene to these areas should be carefully avoided. TAZORAC® Gel was investigated for up to 12 months during clinical trials for psoriasis.

For acne: Cleanse the face gently. After the skin is dry, apply a thin film of TAZORAC® Gel 0.1% (2 mg/cm^2) once a day, in the evening, to the skin where acne lesions appear. Use enough to cover the entire affected area. TAZORAC® Gel was investigated for up to 12 weeks during clinical trials for acne.

HOW SUPPLIED

TAZORAC® (tazarotene) Gel is available in concentration of 0.1%. It is available in a collapsible aluminum tube with a tamper-evident aluminum membrane over the opening and a white propylene screw cap, in 30 gm and 100 gm sizes.

 | TAZORAC® Gel 0.1%
30 gm | NDC 54868-4456-1
100 gm | NDC 54868-4456-0

NOTE: TAZORAC® (tazarotene) Gel should be stored at 25°C (77°F): excursion permitted to 15-30°C (59-86°F).

RX ONLY

® Marks owned by Allergan, Inc.
U.S. Patent Numbers 5,089,509; 5,914,334 and 6,258,830
ALLERGAN
Irvine, California 92612, USA
©2004 Allergan, Inc.

Printed in USA
8606X, 8607XA
January 2004
71722US10P

Relabeling of "Additional Barcode Label" by:
Physicians Total Care, Inc.
Tulsa, OK 74146

Pharmacist: Please cut or tear at dotted line and provide this patient package insert to your customer

- - - - - - - - - - - - - - - - - - - - - - - - - - - - - - - - - - - - - - - - - - - - - - - - - - - - - - - - - - - - - - - - - - - - - - - - - - - - - - - - - - - - - - - - - - - - - - - - - - - - - - - - - - - - - - - - - - - - -

PATIENT INFORMATION

TAZORAC®
(tazarotene) Gel 0.05%
(tazarotene) Gel 0.1%

INFORMATION FOR PATIENTS

Please read this leaflet carefully before you start to use your medicine. Read the information you get every time you get more medicine. There may be new information about the drug. This leaflet does not take the place of talks with your doctor. If you have any questions, or are not sure about anything, ask your doctor or pharmacist.

USES

TAZORAC® Gel 0.05% is used in the treatment of stable plaque psoriasis covering up to 20% of body surface area.

TAZORAC® Gel 0.1% is used in the treatment of stable plaque psoriasis covering up to 20% of body surface area and in the treatment of mild to moderately severe facial acne.

BEFORE YOU USE THIS MEDICINE

You should be aware that:

1. TAZORAC® Gel should not be used if you are pregnant, attempting to become pregnant or at high risk of pregnancy. Consult your physician for adequate birth control measures if you are a female of child-bearing potential. If you are able to become pregnant, take a pregnancy test within 2 weeks prior to beginning to use TAZORAC® Gel to be sure you are not pregnant. If you have menstrual periods, begin taking TAZORAC® Gel during a normal menstrual period. These actions help assure that you are not pregnant when you begin use.
2. TAZORAC® Gel should be used with caution if you are also using other topical agents with a strong skin drying effect, products with high concentrations of alcohol, astringents, spices, the peel of lime, medicated soaps or shampoos, permanent wave solutions, electrolysis, hair depilatories or waxes, or other preparations or processes that might dry or irritate the skin, unless otherwise instructed by your health care practitioner.
3. TAZORAC® Gel should not be used if you have sunburn, eczema or other chronic skin condition(s). TAZORAC® Gel may cause severe irritation if applied to eczematous skin. If you have sunburn, you should wait until full recovery before using TAZORAC® Gel.
4. TAZORAC® Gel should not be used if you are inherently sensitive to sunlight.
5. TAZORAC® Gel should not be used if you are taking other drugs that increase your sensitivity to sunlight (e.g., thiazides, tetracyclines, fluoroquinolones, phenothiazines, sulfonamides). Inform your physician if you are taking any other medications.
6. You should use protective clothing and sunscreens with minimum SPF of 15 during the day when being treated with TAZORAC® Gel . You should avoid direct sun exposure as much as possible and avoid sunlamps totally while being treated with TAZORAC® Gel, unless advised otherwise by your doctor.
7. If you have considerable sun exposure due to occupation, particular caution as described above should be exercised when using TAZORAC® Gel.
8. Weather extremes, such as wind or cold, may be more irritating to your skin while you are using TAZORAC® Gel.

BEFORE YOU USE THIS MEDICINE

Tell your doctor:

1. if you are pregnant or are considering becoming pregnant.
2. if you are breast-feeding. We do not know if tazarotene can pass through the milk to the baby. The potential harm to the baby is unknown.
3. if you are allergic to any ingredients in this medicine.
4. if you are already using other products that make your skin dry.
5. if you have a skin condition called eczema.
6. if you will be subject to excessive sun exposure.
7. if you are taking vitamin A supplements.

HOW TO USE THIS PRODUCT:

- Read the directions on your prescription label carefully. Ask your doctor or pharmacist to explain anything that you do not understand.
- If you become pregnant while using TAZORAC® Gel, you should immediately discontinue its use and contact your doctor.
- If you use a cream or lotion to soften or lubricate your skin, apply TAZORAC® Gel after ensuring that there is no more cream or lotion on the skin.
- With use of TAZORAC® Gel, some people notice a feeling of itching, burning or stinging. If irritation is excessive, consult your health care provider, who may adjust your medication temporarily to a more comfortable level. Effectiveness of this medication when used less often than once daily has not been proven.
- Do not cover treated areas with dressings or bandages.
- Never use more TAZORAC® Gel than instructed and never use it more often than instructed, as application of larger amounts of medication than recommended will not lead to more rapid or better results, and marked redness, peeling or discomfort may occur.
- Wash your hands after applying the medication unless you are treating your hands for psoriasis. If the gel accidentally gets on areas you do not need to treat, wash it off.
- Keep TAZORAC® Gel away from your eyes, eyelids, and mouth. If it gets in contact with your eyes, wash them with large amounts of cool water, and contact a doctor if eye irritation persists.

MISSED DOSES:

- If you forget or miss a dose of TAZORAC® Gel, do not try to "make it up." Return to your normal application schedule as soon as you can.

INSTRUCTIONS SPECIFIC TO TREATMENT OF PSORIASIS:

- If you bathe or shower before using TAZORAC® Gel, be sure the skin is dry before application. Apply a thin film of the gel to your psoriasis lesions once a day before going to bed.
- Carefully avoid application to apparently uninvolved skin. TAZORAC® Gel may be more irritating to non-lesional skin.
- If you need to treat your hands, avoid contact with your eyes.
- Usually your psoriasis plaques and scales will begin to improve in about one to four weeks, but the redness may take longer to improve. Continue to use TAZORAC® Gel as directed by your doctor.
- Contact your doctor if your psoriasis becomes worse.

INSTRUCTIONS SPECIFIC TO TREATMENT OF ACNE:

- Gently clean and dry your face before using TAZORAC® Gel. Apply TAZORAC® Gel once a day, before going to bed, to entire areas of the face where you have acne lesions. Use enough gel to cover the entire affected area with a thin film.
- Follow your doctor's directions for other routine skin care and the use of make-up. Talk to your doctor about the use of sunscreens and cosmetics, especially those that dry your skin.
- Usually, your acne will begin to improve in about 4 weeks. Continue to use TAZORAC® Gel for up to 12 weeks as directed by your doctor.
- Contact your doctor if your acne becomes worse.

POSSIBLE SIDE EFFECTS OF TAZORAC® GEL

For patients with psoriasis, the most common side effects of TAZORAC® Gel 0.05% and 0.1% are itching, burning/stinging, red skin, worsening of psoriasis, irritation, and skin pain.

For patients with acne, the most common side effects of TAZORAC® Gel 0.1% are peeling, burning/stinging, dry skin, red skin, and itching.

Tell your doctor if these side effects become problems. Your doctor may wish to adjust your dose of TAZORAC® Gel. However, effectiveness of TAZORAC® Gel when used less often than once a day has not been proven.

While you take TAZORAC® Gel, weather extremes, such as wind or cold, may irritate your skin more than usual.

WARNINGS:

TAZORAC® Gel should not be used if you are allergic to any of its ingredients. TAZORAC® Gel contains tazarotene as the active ingredient, and the following inactive ingredients: ascorbic acid, benzyl alcohol, butylated hydroxyanisole, butylated hydroxytoluene, carbomer 934P, edetate disodium, hexylene glycol, poloxamer 407, polyethylene glycol 400, polysorbate 40, purified water, and tromethamine.

TAZORAC® Gel should not be used if you are pregnant, attempting to become pregnant or at high risk of pregnancy. Women of child-bearing potential should use adequate birth-control measures when TAZORAC® Gel is used.

If TAZORAC® Gel is swallowed by accident, contact your doctor or a poison control center.

Do not use TAZORAC® Gel after the expiration date found on the bottom seal of the tube.

This medicine is for your use only. It can only be prescribed by a doctor. Never give it to anyone else. It may harm them even if their skin problem appears to be the same as yours.

Retinoids should not be used on eczematous skin, as they may cause severe irritation. Do not use TAZORAC® Gel until your doctor has confirmed that your eczema has fully recovered.

Because of increased burning susceptibility, exposure to sunlight (including sunlamps) should be avoided or minimized during the use of TAZORAC® Gel, unless prescribed differently by your doctor.

You should use sunscreens (minimum SPF of 15) and protective clothing when using TAZORAC® Gel. Be certain that you use these precautions if you expect to experience considerable sun exposure or if you are sensitive to sunlight.

If you have a sunburn, do not use TAZORAC® Gel until you have fully recovered.

Do not use TAZORAC® Gel if you are also taking drugs known to be photosensitizers (e.g., thiazides, tetracyclines, fluoroquinolones, phenothiazines, sulfonamides), unless you have discussed taking both drugs with your doctor, because of the increased possibility of a more severe reaction.

The safety of use over more than 20% of body surface area has not been established in psoriasis or acne.

INSTRUCTIONS FOR USE AND HANDLING: Keep tube tightly closed when not in use. Store it in a safe place where children cannot reach it. TAZORAC® Gel should be stored at 25°C (77°F): excursion permitted to 15-30 °C (59-86°F).

GENERAL ADVICE ABOUT PRESCRIPTION MEDICINES:

This medicine is for your use only. Never give it to other people. It may harm them even if their skin problem appears to be the same as yours. Do not use TAZORAC® Gel for a condition for which it was not prescribed. Do not use TAZORAC® Gel after the expiration date on the bottom seal of the tube.

WHERE CAN I GET MORE INFORMATION ABOUT TAZORAC® GEL?

You can contact Allergan by calling 800-433-8871. You can ask your doctor or pharmacist for the information about TAZORAC® Gel that is written for health professionals.

IF YOU HAVE QUESTIONS ABOUT PSORIASIS: Information is available from:

The National Psoriasis Foundation:
6600 SW 92nd Avenue, Suite 300, Portland, OR 97223-7195.
Telephone: (800) 723-9166, or on the World Wide Web at http://www.psoriasis.org.

® Marks owned by Allergan, Inc.
U.S. Patent Numbers 5,089,509; 5,914,334 and 6,258,830

ALLERGAN
Irvine, California 92612, USA
©2004 Allergan, Inc.
Printed in USA
8606X, 8607XA
January 2004
71722US10P

PRINCIPAL DISPLAY PANEL

TAZORAC®
(tazarotene) Gel 0.1%